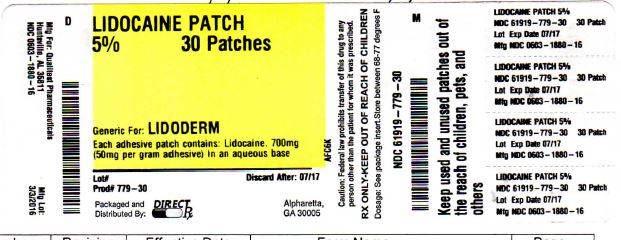 DRUG LABEL: LIDOCAINE
NDC: 61919-779 | Form: PATCH
Manufacturer: DIRECT RX
Category: prescription | Type: HUMAN PRESCRIPTION DRUG LABEL
Date: 20160328

ACTIVE INGREDIENTS: LIDOCAINE 700 mg/1 1
INACTIVE INGREDIENTS: UREA; GLYCERIN; POLYVINYL ALCOHOL; SODIUM POLYACRYLATE (2500000 MW); EDETATE DISODIUM; GELATIN; SORBITOL; POLYACRYLIC ACID (250000 MW); TARTARIC ACID; KAOLIN; METHYLPARABEN; PROPYLENE GLYCOL; PROPYLPARABEN; CARBOXYMETHYLCELLULOSE SODIUM; DIHYDROXYALUMINUM AMINOACETATE

LIDOCAINE PATCH 5%